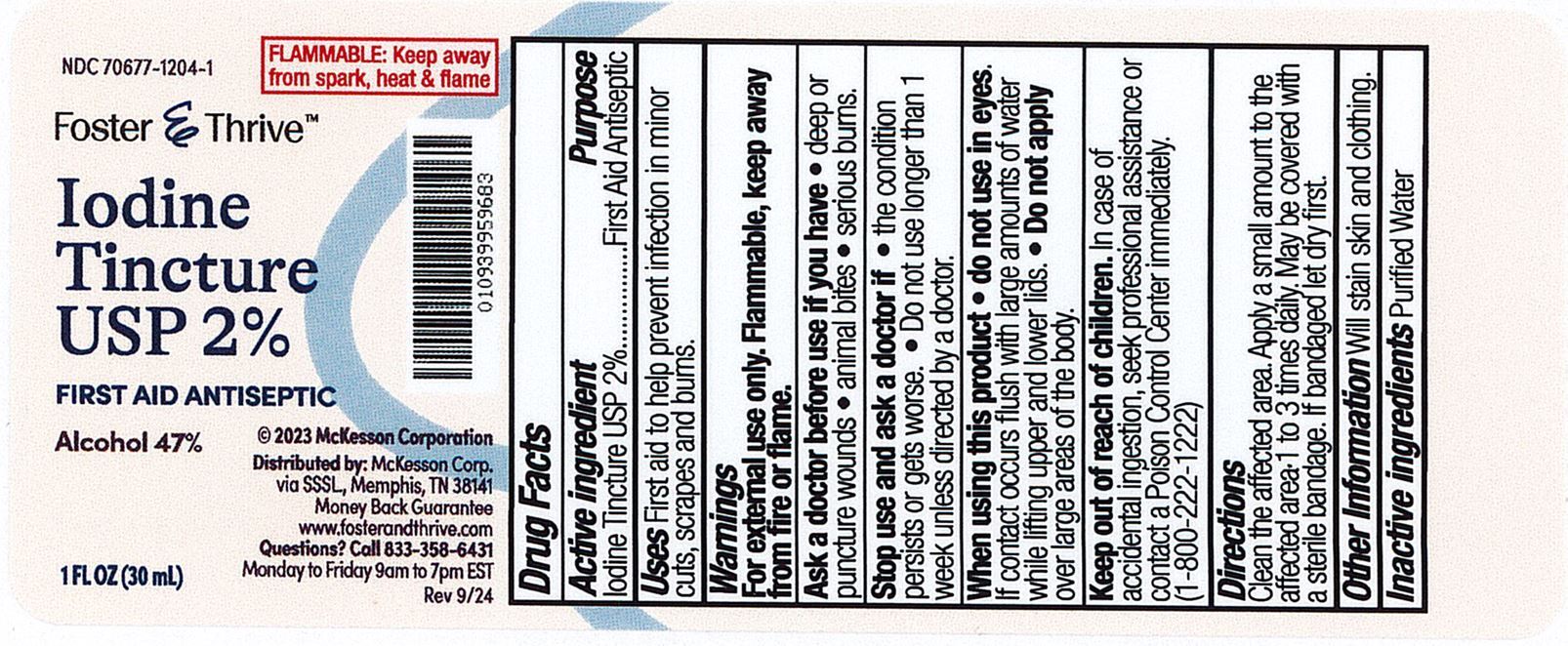 DRUG LABEL: Foster and Thrive 2% Mild Iodine Tincture
NDC: 70677-1204 | Form: LIQUID
Manufacturer: Strategic Sourcing Services, LLC
Category: otc | Type: HUMAN OTC DRUG LABEL
Date: 20241217

ACTIVE INGREDIENTS: SODIUM IODIDE 24 mg/1 mL; IODINE 20 mg/1 mL
INACTIVE INGREDIENTS: WATER; ALCOHOL

Foster & Thrive 2% Mild Iodine Tincture

ACTIVE INGREDIENT

Iodine Tincture USP 2%

PURPOSE

First Aid Antiseptic

INDICATIONS AND USAGE

First aid to help prevent infection in minor cuts, scrapes, and burns.

WARNINGS

For external use only. Flammable, keep away from fire and flame

Keep out of reach of children.If swallowed, get medical help or contact a Poison Control Center immediately. (1-800-222-1222)

INACTIVE INGREDIENT

Purified Water

Ask a doctor before use if you have

- deep or puncture wounds
- animal bites
- serious burns

Stop use and ask a doctor if

the condition persists or gets worse

Do not use longer than 1 week unless directed by a doctor

When using this product

- do not use in eyes.

If contact occurs flush with large amounts of water while lifting upper and lower lids

- Do not apply over large areas of the body

DOSAGE AND ADMINISTRATION

Clearn the affected area

apply a small amount to the affected area 1 to 3 times daily. May be covered with sterile bandage. If bandaged let dry first.